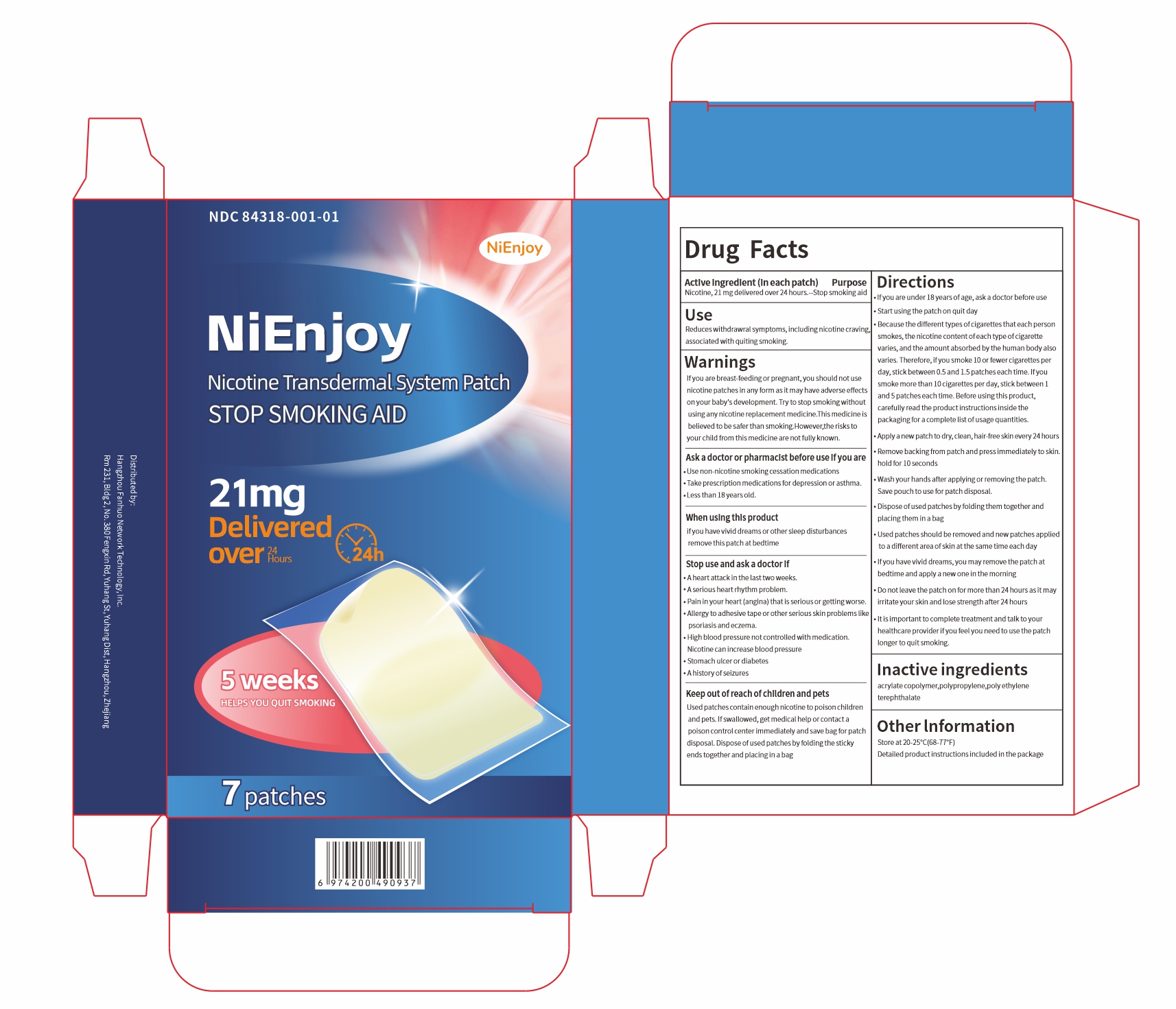 DRUG LABEL: NiEnjoy Nicotine Transdermal System
NDC: 84318-001 | Form: PATCH
Manufacturer: Hangzhou Fanhuo Network Technology Co., Ltd.
Category: otc | Type: HUMAN OTC DRUG LABEL
Date: 20240515

ACTIVE INGREDIENTS: NICOTINE 21 mg/24 h
INACTIVE INGREDIENTS: POLYPROPYLENE (30000 MW); POLYETHYLENE TEREPHTHALATE (INTRINSIC VISCOSITY 0.40-0.70); METHACRYLIC ACID AND ETHYL ACRYLATE COPOLYMER

84318-001

ACTIVE INGREDIENT

Nicotine, 21 mg delivered over 24 hours.

PURPOSE

Stop smoking aid

INDICATIONS AND USAGE

Reduces withdrawral symptoms, including nicotine craving.associated with quiting smoking.

WARNINGS

If you are breast-feeding or pregnant,you should not use nicotine patches in any form asit may have adverse effects onyour baby's development. Try to stopsmoking without using any nicotine replacement medicine.This medicine is believed to be safer than smoking. However,the risks to your child from this medicine arenot fully known.

Ask a doctor or pharmacist before use if you are

Use non-nicotine smoking cessation medications

Take prescription medications for depression or asthma.

Less than 18 years old.

When using this product if you have vivid dreams or other sleep disturbances remove this patch at bedtime

Stop use and ask a doctor if

Aheart attack in the last two weeks.

A serious heart rhythm problem.

Pain in your heart (angina) that is serious or getting worse.

Alergy to adhesive tape or other serious skin problemslike psoriasis and eczema.

High blood pressure not controlled with medication.Nicotine can increaseblood pressure

Stomach ulcer or diabetes

Ahistory of seizures

Keep out of reach of children and petsUsed patches contain enough nicotine to poison children and pets. If swallowed, get medical help or contact a poison control center immediately and save bag for patch disposal. Dispose of used patches by folding the sticky ends together and placing in a bag

Directions

-If youare under 18 years of age,ask a doctor before use.

-Start using the patch on quit day.

-Because the different types of cigarettes that each person smokes, thenicotine content of each type of cigarette varies, and the amount absorbed by thehuman body also varies. Therefore, if you smoke 10 or fewer cigarettes per day,stick between 0.5and 1.5 patches each time. Ifyou smoke more than 10 cigarettes per day, stick between 1 and 5 patches each time. Before using this product, carefully read the product instructions inside the packaging for a complete list of usage quantities.

-Apply anewpatch to dry, dlean, hair-free skin every24 hours.

-Remove backing from patch and press immediately to skin.hold for 10 seconds.

-Wash your hands after applying or removing the patch.Save pouch to use for patch disposal.

- Dispose of used patches by folding them together and placing them in a bag.

-Used patches should be removed and new patches applied to a diflerent area of skin at the same time each day

- If you havevivid dreams, you may remove the patch at bedtime and apply a new one in themorning.

- Do not leave the patch on for more than 24 hours as it may irritate your skin and losestrength after 24 hours

-It is important to complete treatment and talk to your healthcare provider if you feel you need to use the patch longer to quit smoking.

STORAGE AND HANDLING

Store at 20-25℃(68-77°F)

Detailed product instructions included in the package

INACTIVE INGREDIENT

acrylate copolymer,polypropylene,polyethylene terephthalate